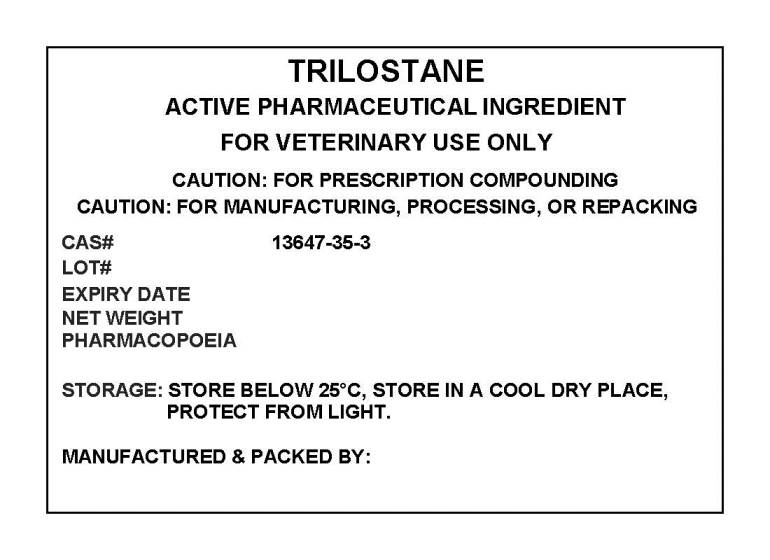 DRUG LABEL: TRILOSTANE
NDC: 72969-074 | Form: POWDER
Manufacturer: PROFESSIONAL GROUP OF PHARMACISTS NEW YORK LLC
Category: other | Type: BULK INGREDIENT
Date: 20210311

ACTIVE INGREDIENTS: TRILOSTANE 1 g/1 g

TRILOSTANE

PACKAGE LABEL

trilostanelabel.jpg